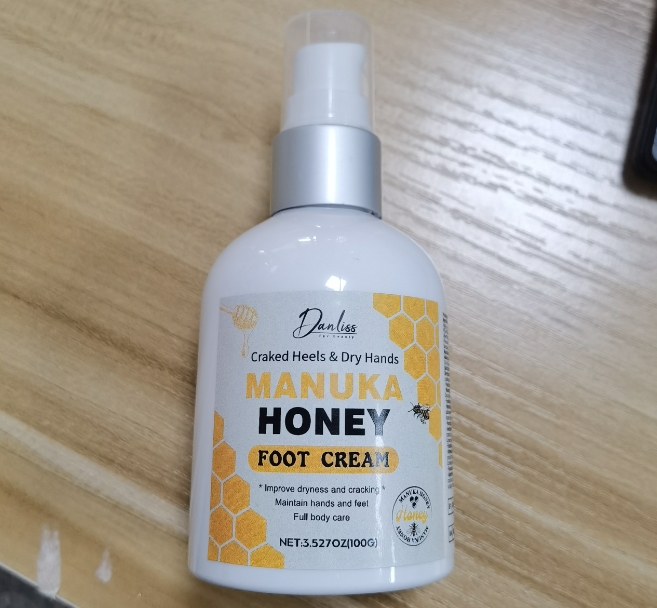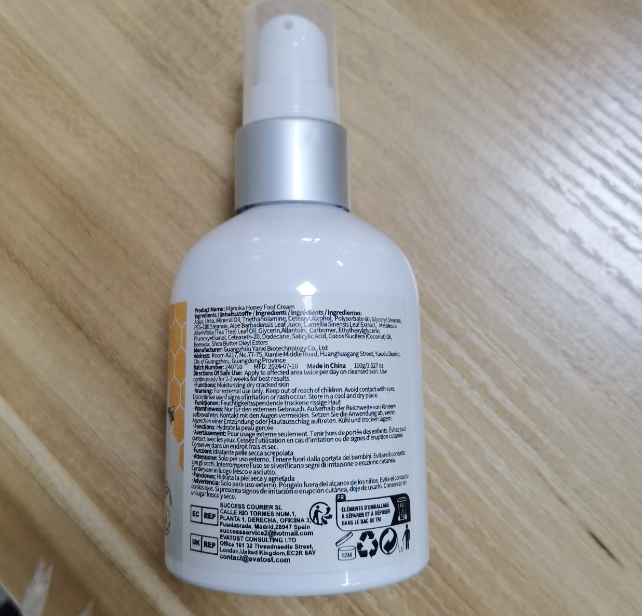 DRUG LABEL: Manuka Honey Foot Cream
NDC: 84025-087 | Form: CREAM
Manufacturer: Guangzhou Yanxi Biotechnology Co., Ltd
Category: otc | Type: HUMAN OTC DRUG LABEL
Date: 20240724

ACTIVE INGREDIENTS: GLYCERIN 3 mg/100 mL; MINERAL OIL 5 mg/100 mL
INACTIVE INGREDIENTS: WATER

DOSAGE AND ADMINISTRATION

Apply to affected area twice per day on cleansed skin.

WARNINGS

keep out of children

INACTIVE INGREDIENT

Aqua

INDICATIONS AND USAGE

Craked Heels & Dry Hands

keep out of children

PURPOSE

Improve dryness and cracking Maintain hands and feet& Full body care